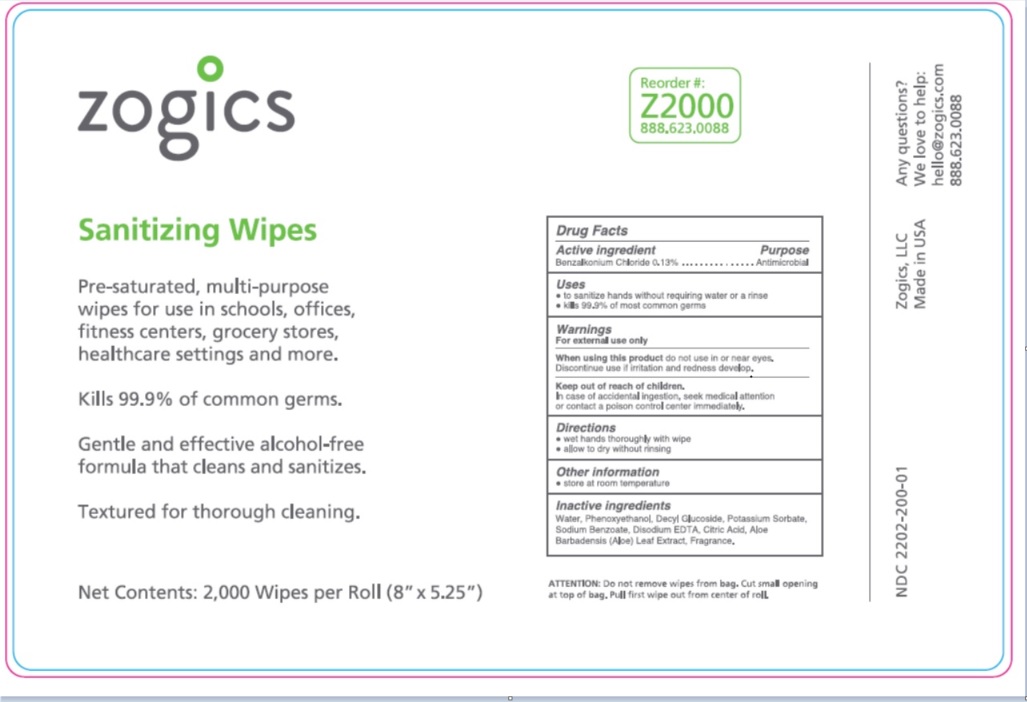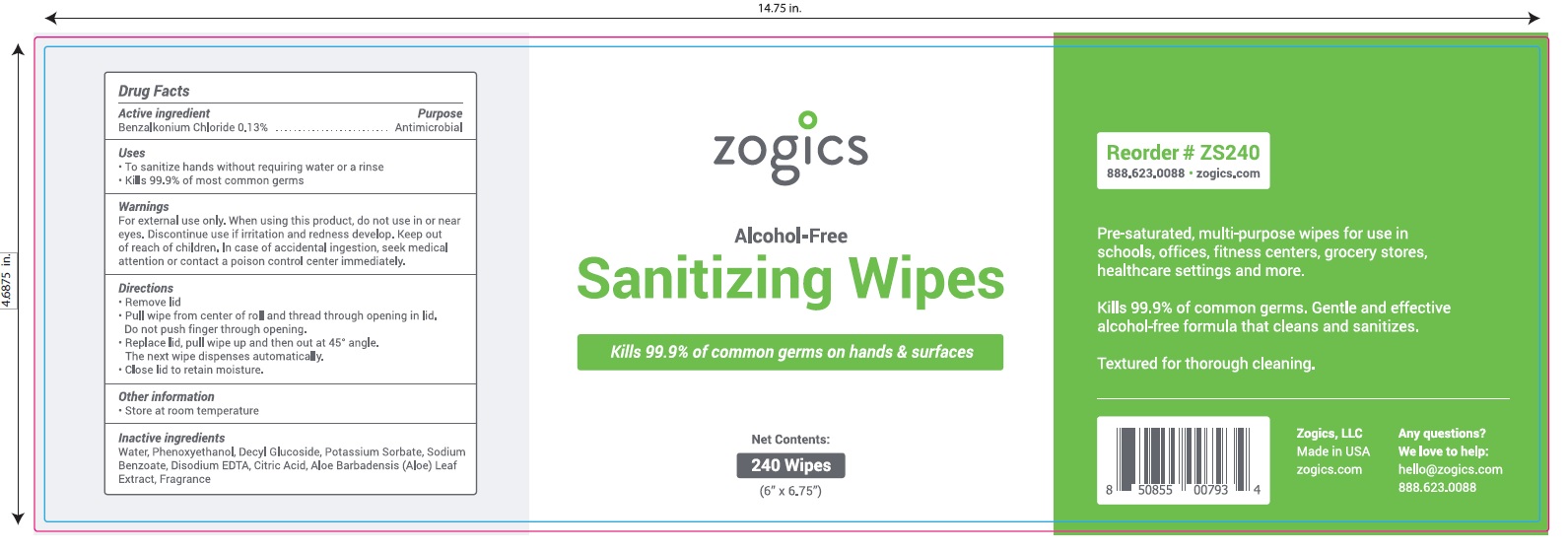 DRUG LABEL: Sanitizing Wipes
NDC: 72202-200 | Form: SWAB
Manufacturer: Zogics, LLC
Category: otc | Type: HUMAN OTC DRUG LABEL
Date: 20251205

ACTIVE INGREDIENTS: BENZALKONIUM CHLORIDE 0.13 g/100 g
INACTIVE INGREDIENTS: WATER; PHENOXYETHANOL; DECYL GLUCOSIDE; POTASSIUM SORBATE; SODIUM BENZOATE; EDETATE DISODIUM; CITRIC ACID MONOHYDRATE; ALOE VERA LEAF

Drug Facts

Active ingredient

Benzalkonium chloride 0.13%

Purpose

Antimicrobial

Uses

- To sanitize hands without requiring water or a rinse
- Kills 99.9% of most common germs

Warnings

For external use only

When using this product

do not use in or near the eyes. Discontinue use if irritation and redness develop

Keep out of reach of children

In case of accidental ingestion, seek medical attention or contact a Poison Control Center immediately.

Directions

- Remove Lid
- Pull wipes from center of roll and thread through opening in lid. Do not push finger through opening.
- Replace lid. Pull wipe up and then out at 45° angle. The next wipe dispenses automatically.
- Close lid to retain moisture.

Other information

Store at room temperature

Inactive ingredients

Water, Phenoxyethanol, Decyl Glucoside, Potassium Sorbate, Sodium Benzoate, Disodium EDTA, Citric Acid, Aloe Barbadensis (Aloe) Leaf Extract, Fragrance

Principal Display Panel

NDC 72202-200-01

2000 count

zogics Sanitizing Wipes

Reorder# Z2000 888.623.0088

Pre-saturated, multipurpose wipes for use in school, offices, fitness centers, grocery stores, healthcare settings and more.

Kills 99.9% of most common germs.

Gentle and effective alcohol-free formula that cleans and sanitizes.

Testured for thorough cleaning

Net Content: 2000 Wipes per Roll (8"X5.25")

Zogics, LLC Made in USA

Any Questions? We love to help: hello@zogicz.com or 888.623.0088

NDC 72202-200-24

zogics

Alcohol- Free

Sanitizing Wipes

Kills 99.9% of common germs on hands and surfaces.

Pre-saturated, multi-purpose wipes for use in schools, offices, fitness centers, grocery stores, healthcare settings and more.

Kills 99.9% of common germs.

Gentle and effective alcohol-free formula that cleans and sanitizes

Textured for thorough cleaning.

Net Contents: 240 Wipes (6" x 6.75")

Zogics, LLC Made in USA

Any Questions? We love to help: hello@zogicz.com or 888.623.0088